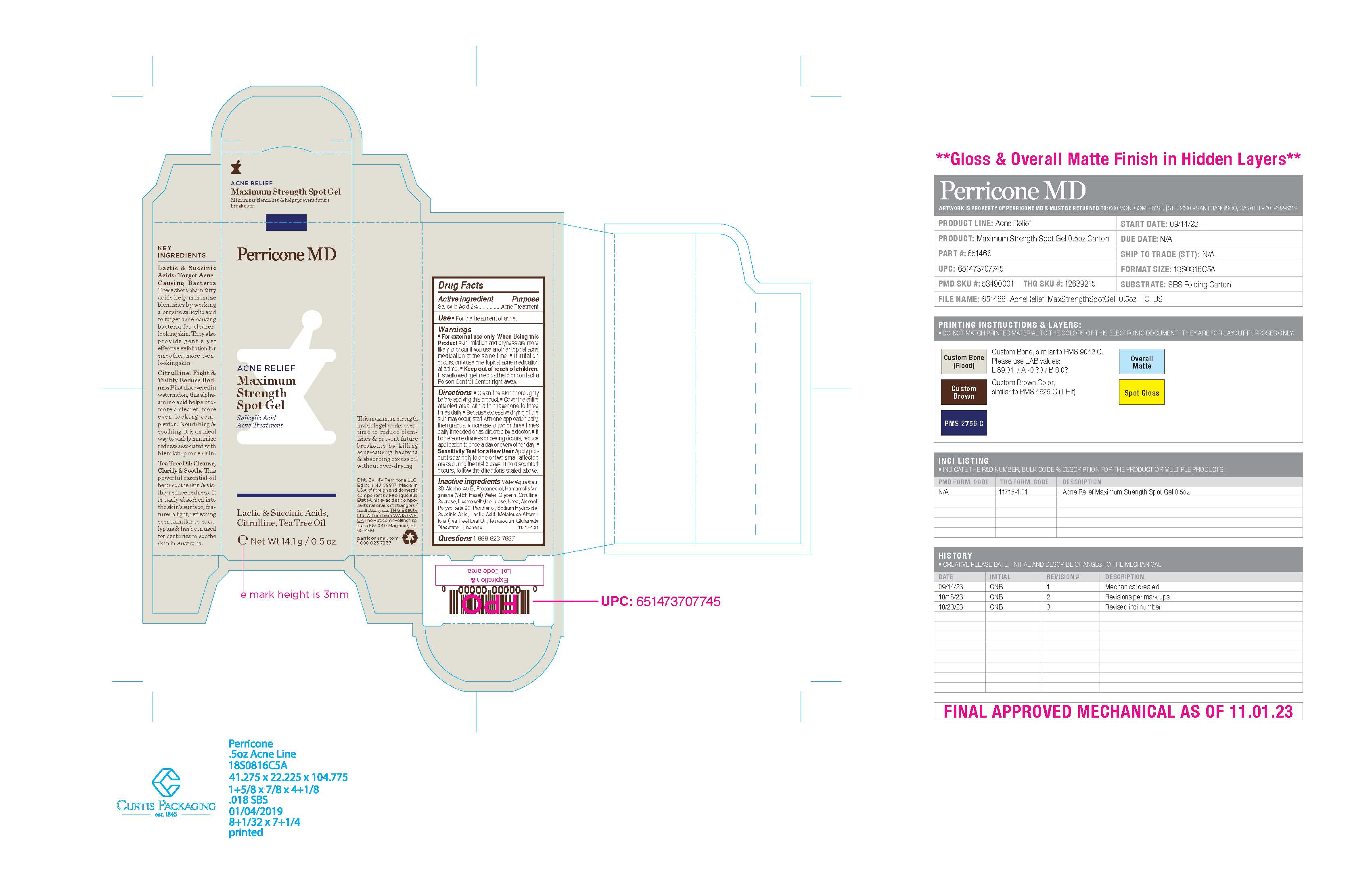 DRUG LABEL: Perricone MD Acne Relief Maximum Strength Spot Gel
NDC: 84448-538 | Form: GEL
Manufacturer: THG Beauty USA LLC
Category: otc | Type: HUMAN OTC DRUG LABEL
Date: 20251107

ACTIVE INGREDIENTS: SALICYLIC ACID 2 g/100 g
INACTIVE INGREDIENTS: POLYSORBATE 20; PANTHENOL; GLYCERIN; SUCROSE; HYDROXYETHYL CELLULOSE, UNSPECIFIED; CITRULLINE; UREA; WATER; TETRASODIUM GLUTAMATE DIACETATE; LACTIC ACID; PROPANEDIOL; WITCH HAZEL; ALCOHOL; LIMONENE, (-)-; SUCCINIC ACID; MELALEUCA ALTERNIFOLIA (TEA TREE) LEAF OIL; SODIUM HYDROXIDE

ACTIVE INGREDIENT

Salicylic Acid 2%

PURPOSE

Acne Treatment

INDICATIONS AND USAGE

For the treatment of acne

WARNINGS

For external use only.

When Using this product skin irritation and dryness are more likely to occur if you use another topical acne medication at the same time.

■ If irritation occurs, only use one topical acne medication at a time.

■ Keep out of reach of children. If swallowed, get medical help or contact a Poison Control Center right away.

Directions

- Clean the skin thoroughly before applying this product.
- Cover the entire affected area with a thin layer one to three times daily.
- Because excessive drying of the skin may occur, start with one application daily, then gradually increase to two or three times

daily if needed or as directed by a doctor.

- If bothersome dryness or peeling occurs, reduce application to once a day or every other day.
- Sensitivity Test for a New User Apply product sparingly to one or two small affected areas during the first 3 days. If no discomfort

occurs, follow the directions stated above.

INACTIVE INGREDIENT

Water/Aqua/Eau, SD Alcohol 40-B, Propanediol, Hamamelis Virginiana (Witch Hazel) Water, Glycerin, Citrulline, Sucrose, Hydroxyethylcellulose, Urea, Alcohol, Polysorbate 20, Panthenol, Sodium Hydroxide, Succinic Acid, Lactic Acid, Melaleuca Alternifolia (Tea Tree) Leaf Oil, Tetrasodium Glutamate Diacetate, Limonene

QUESTIONS

1-888-823-7837